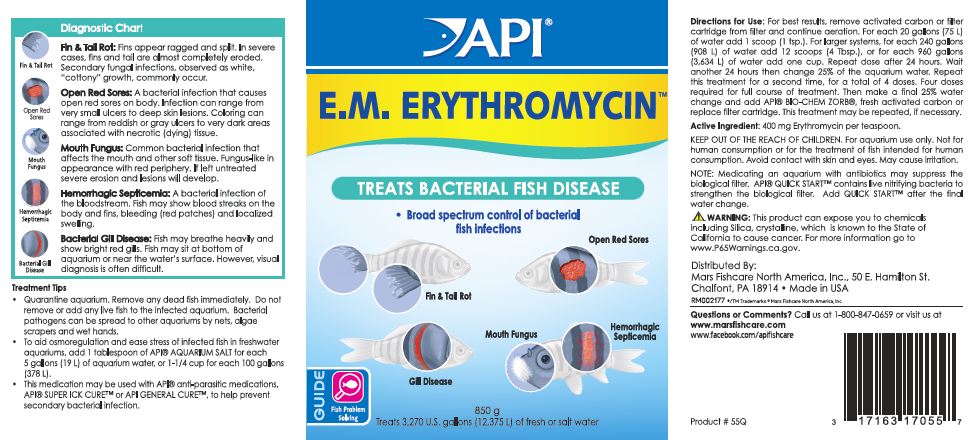 DRUG LABEL: API E.M ERYTHROMYCIN
NDC: 17163-056 | Form: POWDER
Manufacturer: MARS FISHCARE NORTH AMERICA, INC.
Category: animal | Type: OTC ANIMAL DRUG LABEL
Date: 20211229

ACTIVE INGREDIENTS: ERYTHROMYCIN 400 mg/5.2 g

Drug Label

Active Ingredient: 400 mg Erythromycin per teaspoon.

DOSAGE AND ADMINISTRATION

Directions for Use:

For best results, remove activated carbon or filter cartridge from filter and continue aeration.

For each 20 gallons (75 L) of water add 1 scoop (1 tsp.).

For larger systems, for each 240 gallons (908 L) of water add 12 scoops (4 Tbsp.), or for each 960 gallons (3,634 L) of water add one cup.

Repeat dose after 24 hours.

Wait another 24 hours then change 25% of the aquarium water.

Repeat this treatment for a second time, for a total of 4 doses.

Four doses required for full course of treatment.

Then make a final 25% water change and add API BIO-CHEM ZORB, fresh activated carbon or replace filter cartridge.

This treatment may be repeated, if necessary.

WARNINGS AND PRECAUTIONS

KEEP OUT OF THE REACH OF CHILDREN.

For aquarium use only.

Not for human consumption or for the treatment of fish intended for human consumption.

Avoid contact with skin and eyes.

May cause irritation.

Note: Medicating an aquarium with antibiotics may suppress the biological filter. API QUICK START contains live nitrifying bacteria to strengthen the biological filter. Add QUICK START after the final water change.

! WARNING:

This product can expose you to chemicals including Silica, crystalline, which is known to the State of California to cause cancer.

For more information go to wwwP65Warnings.ca.gov.

INDICATIONS AND USAGE

Diagnostic Chart

Fin and Tail Rot:

Fins appear ragged and split. In severe cases, fins,and tail are almost completely eroded. Secondary fungal infections, observed as white, "cottony" growth, commonly occur.

Open Red Sores:

A bacterial infection that causes open red sores on body. Infections can range from very small ulcers to deep skin lesions. Coloring can range from reddish or gray ulcers to very dark areas associated with necrotic (dying) tissue.

Mouth Fungus:

Common bacterial infection that affects the mouth and other soft tissue. Fungus-like in appearance with red periphery. If left untreated severe erosion and lesions will develop.

Hemorrhagic Septicemia:

A bacterial infection of the bloodstream. Fish may show blood streaks on the body and fins, bleeding (red patches) and localized swelling.

Bacterial Gill Disease:

Fish may breath heavily and show bright red gills. Fish may sit at bottom of aquarium or near the water's surface. However, visual diagnosis is often difficult.

Treatment Tips

Quarantine aquarium. Remove any dead fish immediately. Do not remove or add any live fish to the infected aquarium. Bacterial pathogens can be spread to other aquariums by nets, algae scrapers and wet hands.

To aid osmoregulation and ease stress of infected fish in freshwater aquariums, add 1 tablespoon of API AQUARIUM SALT for each 5 gallons (19 L) of aquarium water, or 1-1/4 cup for each 100 gallons (378 L).

This medication may be used with API anti-parasitic medications, API SUPER ICK CURE or API GENERAL CURE, to help prevent secondary bacterial infection.

PACKAGE LABEL

API

E.M. ERYTHROMYCIN

TREATS BACTERIAL FISH DISEASE

Broad spectrum control of bacterial

fish inspections

Fin and Tail Rot

Open Red Sores

Gill Disease

Mouth Fungus

Hemorrhagic

Septicemia

GUIDE

Fish Problem

Solving

850 g

Treats 3,270 U.S. gallons (12,375 L) of fresh or salt water.